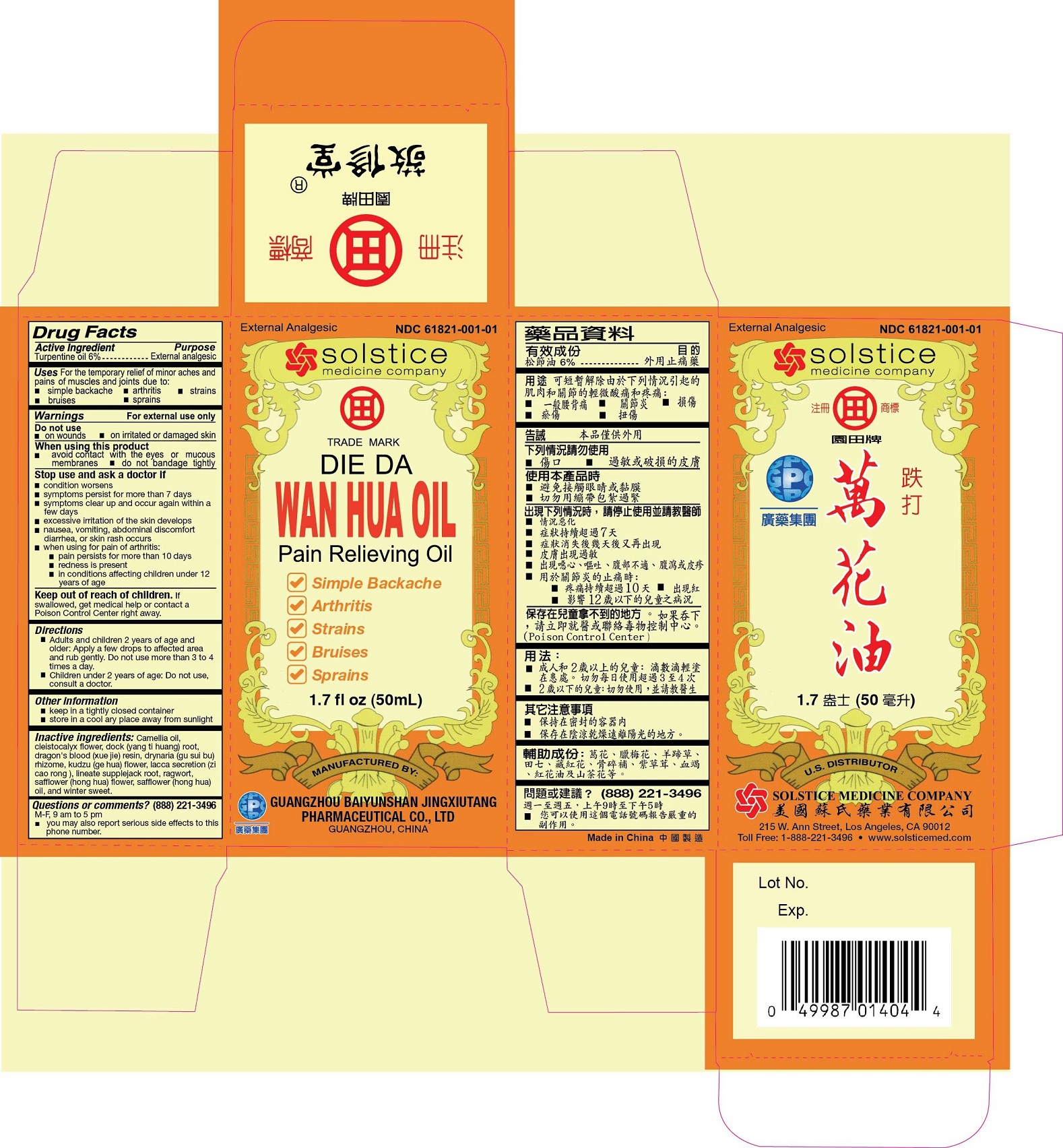 DRUG LABEL: DIE DA WAN HUA PAIN RELIEVING
NDC: 61821-001 | Form: OIL
Manufacturer: GUANGZHOU BAIYUNSHAN JINGXIUTANG PHARMACEUTICAL CO., LTD
Category: otc | Type: HUMAN OTC DRUG LABEL
Date: 20191113

ACTIVE INGREDIENTS: TURPENTINE 6 g/100 mL
INACTIVE INGREDIENTS: CAMELLIA OIL; SYZYGIUM NERVOSUM FLOWER BUD; RUMEX JAPONICUS ROOT; DRAGON'S BLOOD; DRYNARIA FORTUNEI WHOLE; PUERARIA MONTANA VAR. LOBATA FLOWERING TOP; SHELLAC; BERCHEMIA LINEATA ROOT; SAFFLOWER; SAFFLOWER OIL; CHIMONANTHUS PRAECOX WHOLE

Drug Facts

Active ingredient
Turpentine oil 6%

Purpose
External analgesic

Uses
For the temporary relief of minor aches and pains of muscles and joints due to:

- simple backache
- arthritis
- strains
- bruises
- sprains

Warnings
For external use only

Do not use

- on wounds
- on irritated or damaged skin

When using this product
avoid contact with the eyes or mucous membranes
do not bandage tightly

Stop use and ask a doctor if

- condition worsens symptoms persist for more than 7 days
- symptoms clear up and occur again within a few days
- excessive irritation of the skin develops
- nausea, vomiting, abdominal discomfort, diarrhea, or skin rash occurs
- when using for pain of arthritis:
  - pain persists for more than 10 days
  - redness is present
  - in conditions affecting children under 12 years of age

Keep out of reach of children. If swallowed, get medical help or contact a Poison Control Center right away.

Directions

- Adults and children 2 years of age and older: Apply a few drops to affected area and rub gently. Do not use more than 3 to 4 times a day.
- Children under 2 years of age: Do not use, consult a doctor.

Other information

- keep in a tightly closed container
- store in a cool dry place away from sunlight

Inactive ingredients
Camellia (Tsubaki oil) oil, cleistocalyx (Cleistocalyx operculatus) flower, dock (yang ti huang) root, dragon’s blood (xue jie) resin, drynaria (gu sui bu) rhizome, kudzu (ge hua) flower, lacca secretion (zi cao rong), lineate supplejack (Berchemia lineata) root, ragwort (Senecio palmatus), safflower (hong hua) flower, safflower (hong hua) oil, and winter sweet.

Questions or comments?(888) 221-3496 M-F 9 am to 5 pm

PACKAGE LABEL

DIE DA WAN HUA PAIN RELIEVING OIL
External Analgesic
NDC 61821-001-01
1.69 fl oz (50 mL)